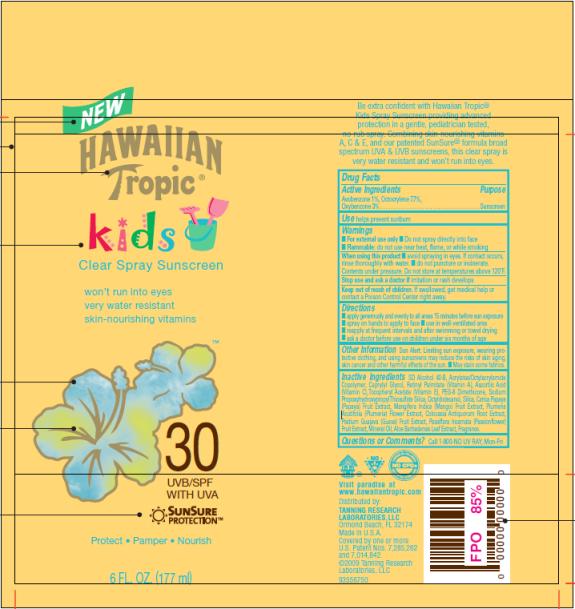 DRUG LABEL: Hawaiian Tropic Kids SPF 30
NDC: 17630-2036 | Form: SPRAY
Manufacturer: Accra-Pac, Inc.
Category: otc | Type: HUMAN OTC DRUG LABEL
Date: 20100328

ACTIVE INGREDIENTS: AVOBENZONE 0.01 mL/1 mL; OCTOCRYLENE 0.077 mL/1 mL; OXYBENZONE 0.03 mL/1 mL
INACTIVE INGREDIENTS: CAPRYLYL GLYCOL; VITAMIN A PALMITATE; ASCORBIC ACID; .ALPHA.-TOCOPHEROL ACETATE, D-; OCTYLDODECANOL; SILICON DIOXIDE; PAPAYA; MANGO; PLUMERIA EXTRACT; GUAVA; PASSION FLOWER EXTRACT; MINERAL OIL; ALOE VERA LEAF

Hawaiian Tropic Kids SPF 30

Drug Facts

Active Ingredients

Avobenzone 0.01mL / 1mL

Octocrylene 0.077mL / 1mL

Oxybenzone 0.03mL / 1mL

Purpose

Sunscreen

Use

helps prevent sunburn

Warnings

- For external use only
- Do not spray directly into face
- Flammable: do not use near heat, flame, or while smoking

When using this product

- avoid spraying in eyes. If contact occurs, rinse thoroughly with water.
- do not puncture or incinerate. Contents under pressure. Do not store at temperatures above 120°F.

Stop use and ask a doctor if

irritation or rash develops

Keep out of reach of children.

If swallowed, get medical help or contact a Poison Control Center right away.

Directions

- apply generously and evenly to all areas 15 minutes before sun exposure
- spray on hands to apply to face
- use in well-ventilated area
- reapply at frequent intervals and after swimming or towel drying
- ask a doctor before use on children under six months of age

Other Information

Sun Alert: Limiting sun exposure, wearing protective clothing, and using sunscreens may reduce the risks of skin aging, skin cancer and other harmful effects of the sun.

- May stain some fabrics.

Inactive Ingredients

SD Alcohol 40-B, Acrylates/Octylacrylamide Copolymer, Caprylyl Glycol, Retinyl Palmitate (Vitamin A), Ascorbic Acid (Vitamin C), Tocopheryl Acetate (Vitamin E), PEG-8 Dimethicone, Sodium Propoxyhydroxypropyl Thiosulfate Silica, Octyldodecanol, Silica, Carica Papaya (Papaya) Fruit Extract, Mangifera Indica (Mango) Fruit Extract, Plumeria Acutifolia (Plumeria) Flower Extract, Colocasia Antiquorum Root Extract, Psidium Guajava (Guava) Fruit Extract, Passiflora Incarnata (Passionflower) Fruit Extract, Mineral Oil, Aloe Barbadensis Leaf Extract, Fragrance.

Questions or Comments?

Call 1-800-NO UV RAY, Mon-Fri

Distributed by:
TANNING RESEARCH
LABORATORIES,LLC
Ormond Beach, FL 32174
Made in U.S.A.

PRINCIPAL DISPLAY PANEL

NEW
HAWAIIAN
Tropic®
kids
Clear Spray Sunscreen
won’t run into eyes
very water resistant
skin-nourishing vitamins
30
UVB/SPF
WITH UVA
SunSure
Protection TM
Protect Pamper Nourish
6 FL. OZ. (177 ml)